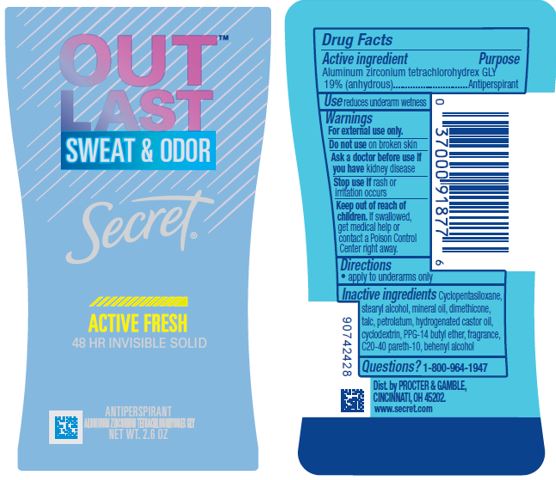 DRUG LABEL: Secret Outlast Invisible Active Fresh
NDC: 69423-476 | Form: STICK
Manufacturer: The Procter & Gamble Manufacturing Company
Category: otc | Type: HUMAN OTC DRUG LABEL
Date: 20200701

ACTIVE INGREDIENTS: ALUMINUM ZIRCONIUM TETRACHLOROHYDREX GLY 19 g/100 g
INACTIVE INGREDIENTS: CYCLOMETHICONE 5; STEARYL ALCOHOL; MINERAL OIL; DIMETHICONE; TALC; PETROLATUM; HYDROGENATED CASTOR OIL; PPG-14 BUTYL ETHER; C20-40 PARETH-10; DOCOSANOL; BETADEX

Secret® Outlast™ Invisible
Active Fresh

Drug Facts

Active ingredient

Aluminum zirconium tetrachlorohydrex Gly 19% (anhydrous)

Purpose

Antiperspirant

Use

reduces underarm wetness

Warnings

For external use only.

Do not use on broken skin

Ask a doctor before use if you have kidney disease

Stop use if rash or irritation occurs

Keep out of reach of children. If swallowed, get medical help or contact a Poison Control Center right away.

Directions

apply to underarms only

Inactive ingredients

cyclopentasiloxane, stearyl alcohol, mineral oil, dimethicone, talc, petrolatum, hydrogenated castor oil, cyclodextrin, PPG-14 butyl ether, fragrance, C20-40 pareth-10, behenyl alcohol

Questions?

1-800-964-1947

Dist. by PROCTER & GAMBLE,
CINCINNATI, OH 45202.

PRINCIPAL DISPLAY PANEL - 73 g Cylinder Label

Secret®

OUTLAST™

ACTIVE FRESH

48 HR INVISIBLE SOLID

ALUMINUM ZIRCONIUM TETRACHLOROHYDREX GLY
ANTIPERSPIRANT

NET WT. 2.6 OZ